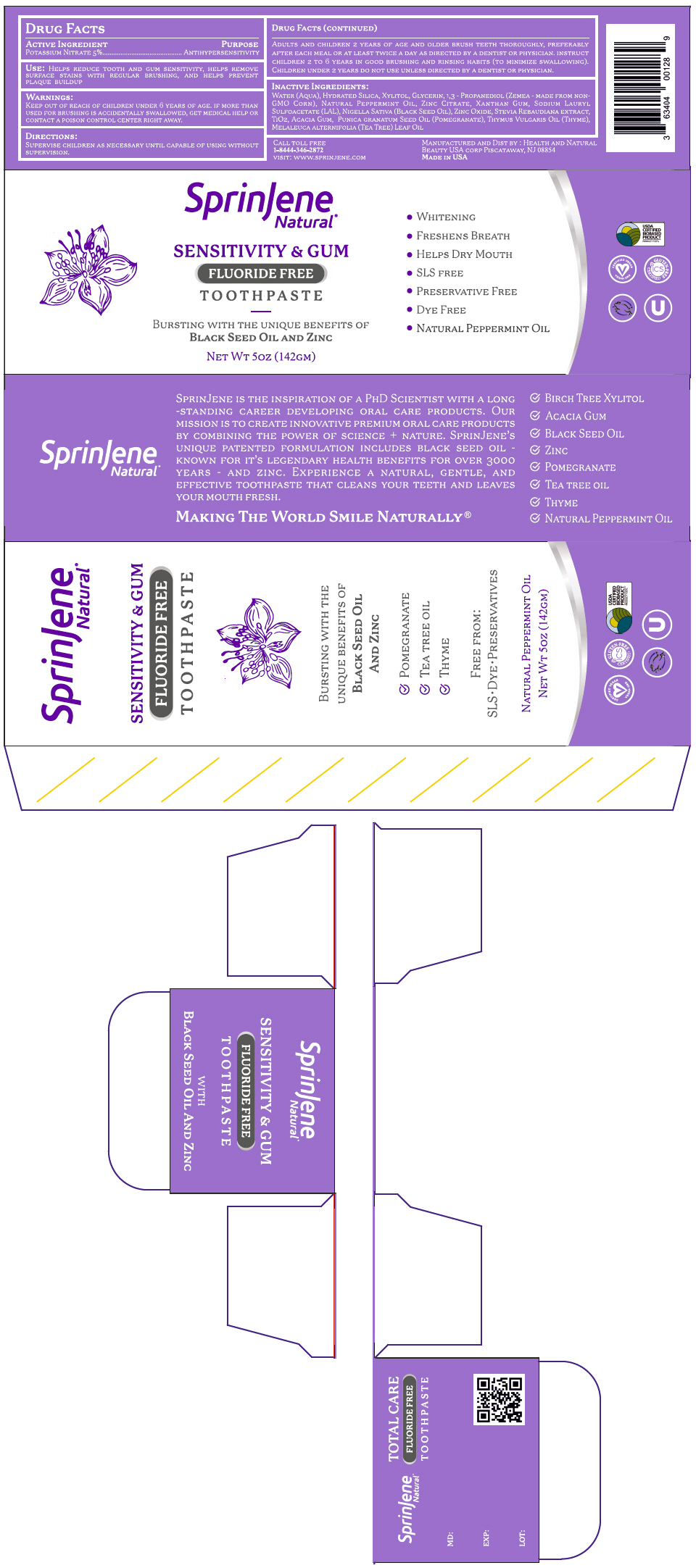 DRUG LABEL: SprinJene Natural 
NDC: 63404-1984 | Form: PASTE, DENTIFRICE
Manufacturer: Health and Natural Beauty USA Corp
Category: otc | Type: HUMAN OTC DRUG LABEL
Date: 20250707

ACTIVE INGREDIENTS: Potassium Nitrate 50 mg/1 g
INACTIVE INGREDIENTS: Water; Hydrated Silica; XYLITOL; Glycerin; PROPANEDIOL; Zinc Citrate; Xanthan Gum; SODIUM LAURYL SULFOACETATE; NIGELLA SATIVA SEED OIL; Zinc Oxide; STEVIA SERRATA FLOWER OIL; Titanium Dioxide; Acacia; POMEGRANATE; THYME OIL; TEA TREE OIL

SprinJene Natural®
Sensitivity & Gum

DRUG FACTS

ACTIVE INGREDIENT

POTASSIUM NITRATE 5%

PURPOSE

ANTIHYPERSENSITIVITY

USE

HELPS REDUCE TOOTH AND GUM SENSITIVITY, HELPS REMOVE SURFACE STAINS WITH REGULAR BRUSHING, AND HELPS PREVENT PLAQUE BUILDUP

WARNINGS

KEEP OUT OF REACH OF CHILDREN UNDER 6 YEARS OF AGE. IF MORE THAN USED FOR BRUSHING IS ACCIDENTALLY SWALLOWED, GET MEDICAL HELP OR CONTACT A POISON CONTROL CENTER RIGHT AWAY.

DIRECTIONS

SUPERVISE CHILDREN AS NECESSARY UNTIL CAPABLE OF USING WITHOUT SUPERVISION.

ADULTS AND CHILDREN 2 YEARS OF AGE AND OLDER BRUSH TEETH THOROUGHLY, PREFERABLY AFTER EACH MEAL OR AT LEAST TWICE A DAY AS DIRECTED BY A DENTIST OR PHYSICIAN. INSTRUCT CHILDREN 2 TO 6 YEARS IN GOOD BRUSHING AND RINSING HABITS (TO MINIMIZE SWALLOWING). CHILDREN UNDER 2 YEARS DO NOT USE UNLESS DIRECTED BY A DENTIST OR PHYSICIAN.

INACTIVE INGREDIENTS

WATER (AQUA), HYDRATED SILICA, XYLITOL, GLYCERIN, 1,3 - PROPANEDIOL (ZEMEA - MADE FROM NON-GMO CORN), NATURAL PEPPERMINT OIL, ZINC CITRATE, XANTHAN GUM, SODIUM LAURYL SULFOACETATE (LAL), NIGELLA SATIVA (BLACK SEED OIL), ZINC OXIDE, STEVIA REBAUDIANA EXTRACT, TIO2, ACACIA GUM, PUNICA GRANATUM SEED OIL (POMEGRANATE), THYMUS VULGARIS OIL (THYME), MELALEUCA ALTERNIFOLIA (TEA TREE) LEAF OIL

MANUFACTURED AND DIST BY : HEALTH AND NATURAL
BEAUTY USA CORP PISCATAWAY, NJ 08854

PRINCIPAL DISPLAY PANEL - 142 GM Tube Carton

SprinJene
Natural®

SENSITIVITY & GUM

FLUORIDE FREE

TOOTHPASTE

BURSTING WITH THE UNIQUE BENEFITS OF
BLACK SEED OIL AND ZINC

- WHITENING
- FRESHENS BREATH
- HELPS DRY MOUTH
- SLS FREE
- PRESERVATIVE FREE
- DYE FREE
- NATURAL PEPPERMINT OIL

USDA
CERTIFIED
BIOBASED
PRODUCT
PRODUCT 100%

CERTIFIED VEGAN
VEGAN.ORG

GLUTEN-FREE
CERTIFIED

NET WT 5OZ (142GM)